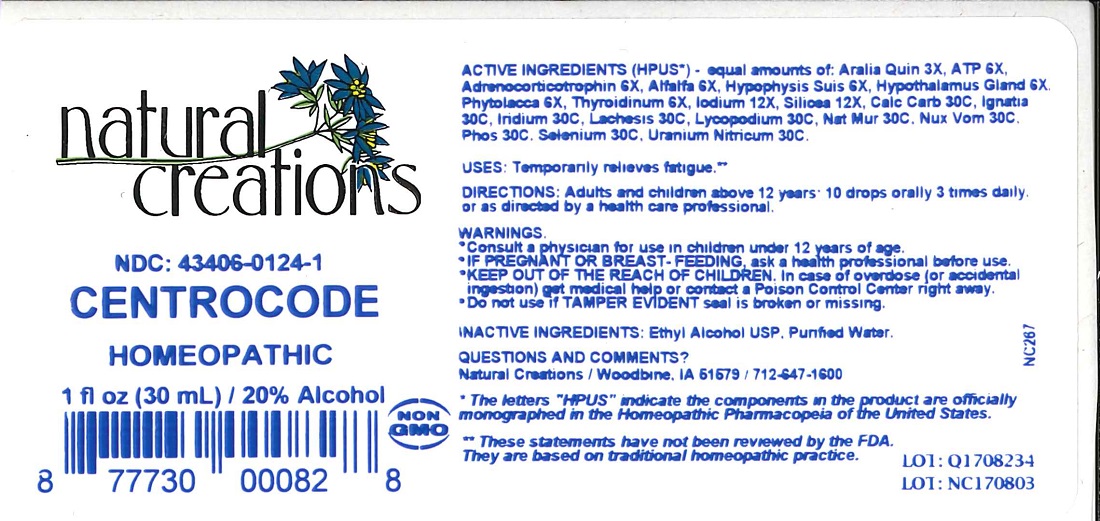 DRUG LABEL: CENTROCODE
NDC: 43406-0124 | Form: LIQUID
Manufacturer: Natural Creations, Inc.
Category: homeopathic | Type: HUMAN OTC DRUG LABEL
Date: 20211115

ACTIVE INGREDIENTS: AMERICAN GINSENG 3 [hp_X]/1 mL; ADENOSINE TRIPHOSPHATE 6 [hp_X]/1 mL; CORTICOTROPIN 6 [hp_X]/1 mL; ALFALFA 6 [hp_X]/1 mL; BOS TAURUS HYPOTHALAMUS 6 [hp_X]/1 mL; PHYTOLACCA AMERICANA ROOT 6 [hp_X]/1 mL; BOS TAURUS PITUITARY GLAND, POSTERIOR 6 [hp_X]/1 mL; THYROID, UNSPECIFIED 6 [hp_X]/1 mL; IODINE 12 [hp_X]/1 mL; SILICON DIOXIDE 12 [hp_X]/1 mL; OYSTER SHELL CALCIUM CARBONATE, CRUDE 30 [hp_C]/1 mL; STRYCHNOS IGNATII SEED 30 [hp_C]/1 mL; IRIDIUM 30 [hp_C]/1 mL; LACHESIS MUTA VENOM 30 [hp_C]/1 mL; LYCOPODIUM CLAVATUM SPORE 30 [hp_C]/1 mL; SODIUM CHLORIDE 30 [hp_C]/1 mL; STRYCHNOS NUX-VOMICA SEED 30 [hp_C]/1 mL; PHOSPHORUS 30 [hp_C]/1 mL; SELENIUM 30 [hp_C]/1 mL; URANYL NITRATE HEXAHYDRATE 30 [hp_C]/1 mL
INACTIVE INGREDIENTS: WATER; ALCOHOL

CENTROCODE

ACTIVE INGREDIENT

ACTIVE INGREDIENTS (HPUS*) - equal amounts of: Aralia Quin 3X, ATP 6X, Adrenocorticotrophin 6X, Alfalfa 6X, Iodium 12X, Silicea 12X, Calc Carb 30C, Ignatia 30C, Iridium 30C, Lachesis 30C, Lycopodium 30C, Nat Mur 30C, Nux Vom 30C, Phos 30C, Selenium 30C, Uranium Nitricum 30C.

PURPOSE

USES: Temporarily relieves fatigue.**

INDICATIONS AND USAGE

USES: Temporarily relieves fatigue.**

DOSAGE AND ADMINISTRATION

DIRECTIONS: Adults & children above 12 years: 10 drops orally 3 times daily, or as directed by a health care professional.

WARNINGS:

* Consult a physician for use in children under 12 years of age.

* IF PREGNANT OR BREAST-FEEDING, ask a health care professional before use.

* KEEP OUT OF THE REACH OF CHILDREN. In case of overdose (or accidental ingestion) get medical help or contact a Poison Control Center right away.

* Do not use if TAMPER EVIDENT seal is broken or missing.

KEEP OUT OF REACH OF CHILDREN

KEEP OUT OF THE REACH OF CHILDREN. In case of overdose (or accidental ingestion) get medical help or contact a Poison Control Center right away.

INACTIVE INGREDIENTS: Ethyl Alcohol USP, Purified Water.

QUESTIONS & COMMENTS?

Natural Creations, Inc. / Woodbine, IA 51579 / 712-647-1600

REFERENCES

* The letters "HPUS" indicate the components in the product are officially monographed in the Homeopathic Pharmacopeia of the United States.

** These statements have not been reviewed by the FDA. They are based on traditional homeopathic practice.

LOT:

PACKAGE LABEL

NDC: 43406-0124-1

CENTROCODE

HOMEOPATHIC

1 fl oz (30 mL) / 20% Alcohol

UPC: 877730000828